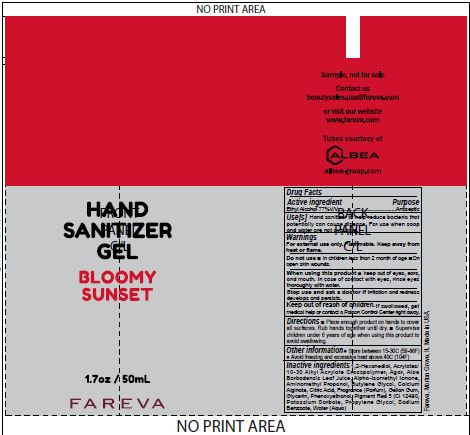 DRUG LABEL: Hand Sanitizer
NDC: 72686-186 | Form: GEL
Manufacturer: Fareva Morton Grove, Inc.
Category: otc | Type: HUMAN OTC DRUG LABEL
Date: 20201215

ACTIVE INGREDIENTS: ALCOHOL 77 mL/100 mL
INACTIVE INGREDIENTS: PHENOXYETHANOL; PIGMENT RED 5; CITRIC ACID MONOHYDRATE; SODIUM BENZOATE; POTASSIUM SORBATE; ALOE; AMINOMETHYLPROPANOL; GELLAN GUM (LOW ACYL); CALCIUM ALGINATE; CARBOMER INTERPOLYMER TYPE A (55000 CPS); BUTYLENE GLYCOL; PROPYLENE GLYCOL; 1,2-HEXANEDIOL; AGAR; GLYCERIN; FRAGRANCE ORANGE ORC2000765; WATER

1. Alcohol (ethanol) (USP or Food Chemical Codex (FCC) grade) (77%, volume/volume (v/v)) in an aqueous solution denatured according to Alcohol and Tobacco Tax and Trade Bureau regulations in 27 CFR part 20.
2. Glycerin
3. FRAGRANCE (PARFUM)
  d. ACRYLATES/C10-30 ALKYL ACRYLATE CROSSPOLYMER
  e. BUTYLENE GLYCOL
  f. ALOE BARBADENSIS LEAF JUICE
  g. AMINOMETHYL PROPANOL
  h. 1,2-HEXANEDIOL
  i. AGAR
  j. GELLAN GUM
  k. CALCIUM ALGINATE
  l. PHENOXYETHANOL
  m. PROPYLENE GLYCOL
  n. PIGMENT RED 5 (CI 12490)
  o. CITRIC ACID
  p. SODIUM BENZOATE
  q. POTASSIUM SORBATE

RECENT MAJOR CHANGES

Content was updated to match the final formula.

Active Ingredient(s)

Alcohol 77% v/v. Purpose: Antiseptic

Purpose

Antiseptic

Use

Hand Sanitizer to help reduce bacteria that potentially can cause disease. For use when soap and water are not available.

Warnings

For external use only. Flammable. Keep away from heat or flame

Do not use

- in children less than 2 months of age
- on open skin wounds

When using this product keep out of eyes, ears, and mouth. In case of contact with eyes, rinse eyes thoroughly with water.

Stop use and ask a doctor if irritation and redness develops and persists.

Keep out of reach of children. If swallowed, get medical help or contact a Poison Control Center right away.

Directions

- Place enough product on hands to cover all surfaces. Rub hands together until dry.
- Supervise children under 6 years of age when using this product to avoid swallowing.

Other information

- Store between 15-30C (59-86F)
- Avoid freezing and excessive heat above 40C (104F)

Inactive ingredients

1,2-Hexanediol, Acrylates/C10-30 Alkyl Acrylate Crosspolymer, Agar, Aloe Barbadensis Leaf Juice, Alpha-Isomethyl Ionone,
Aminomethyl Propanol, Butylene Glycol, Calcium Alginate, Citric Acid, Fragrance (Parfum), Gellan Gum, Glycerin, Phenoxyethanol, Pigment Red 5 (Ci 12490, Potassium Sorbate, Propylene Glycol, Sodium Benzoate, Water (Aqua)

Package Label - Principal Display Panel

50 mL NDC: 72686-186-05